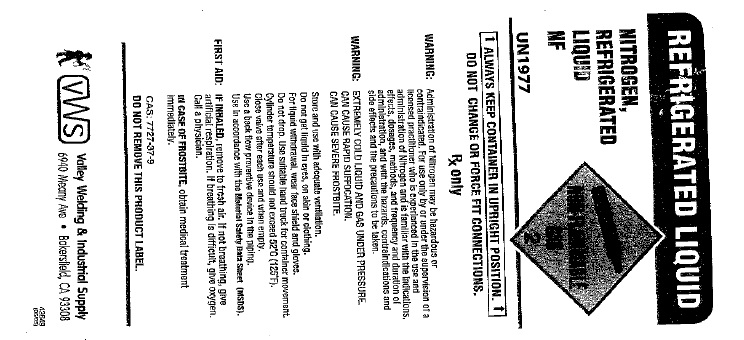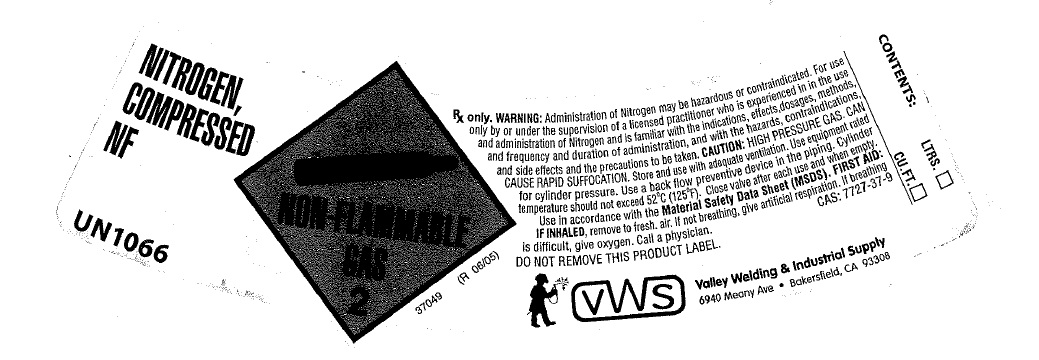 DRUG LABEL: Nitrogen
NDC: 42924-002 | Form: GAS
Manufacturer: Terjan Co., Inc. DBA Valley Welding Supply Company
Category: prescription | Type: HUMAN PRESCRIPTION DRUG LABEL
Date: 20100402

ACTIVE INGREDIENTS: Nitrogen 990 mL/1 L

nitrogen

PACKAGE LABEL

REFRIGERATED LIQUID
NITROGEN, REFRIGERATED LIQUID NF
UN 1977
NON-FLAMMABEL GAS 2
ALWAYS KEEP CONTAINER IN UPRIGHT POSITION
DO NOT CHANGE OR FORCE FIT CONNECTIONS. RX only.
WARNING: Administration of Nitrogen may be hazardous or contraindicated. For use only by or under the supervision of a licensed practitioner who is experienced in the use and administration of Nitrogen and is familiar with the indications, effects, dosages, methods, and frequency and duration of administration, and with the hazards, contraindications and side effects and the precautions to be taken.
WARNING: EXTREMELY COLD LIQUID AND GAS UNDER PRESSURE. CAN CAUSE RAPID SUFFOCATION. CAN CAUSE SEVERE FROSTBITE.
Store and use with adequate ventilation. Do not get liquid in eyes, on skin or clothing. For liquid withdrawal, wear face shield and gloves. Do not drop. Use suitable hand truck for container movement. Cylinder temperature should not exceed 52 degrees C (125 degrees F). close valve after each use and when empty. Use a back flow preventive device in the piping. Use in accordance with the Material Safety Data Sheet (MSDS).
FIRST AID: IF INHALED, remove to fresh air. If not breathin, give artificial respiration. If breathing is difficult, give oxygen. Call a physician.
IN CASE OF FROSTBITE, obtain medical treatment immediately.
CAS: 7727-37-9
DO NOT REMOVE THIS PRODUCT LABEL
VWS Valley Welding and Industrial Supply
6940 Meany Ave
Bakersfield, CA 93308

PACKAGE LABEL

NITROGEN COMPRESSED NF
FLAMMABLE GAS 2
UN 1066
RX ONLY. WARNING: administration of Nitrogen may be hazardous or contraindicated. For use only by or under the supervision of a licensed practitioner who is experienced in the use and administration of Nitrogen and is familiar with the indications, effects, dosages, methods, and frequency and duration of administration, and with the hazards, contraindications, and side effects and the precautions to be taken. CAUTION: HIGH PRESSURE GAS. CAN CAUSE RAPID SUFFOCATION. Store and use with adequate ventilation. Use equipment rated for cylinder pressure. Use a back flow preventative device in the piping. Cylinder temperature should not exceed 52 degrees C (125 degrees F). Close valve after each use and when empty. Use in accordance with the Material Safety Data Sheet (MSDS). FIRST AID: IF INHALED, remove to fresh air. If not breathing, give artificial respiration. If breathing is difficult, give oxygen. Call a physician. CAS: 7727-37-9 DO NOT REMOVE THIS PRODUCT LABEL
CONTENTS: LITERS. CU. FT.
VWS Valley Welding and Industrial Supply
6940 Meany Ave. Bakersfield, CA 93308